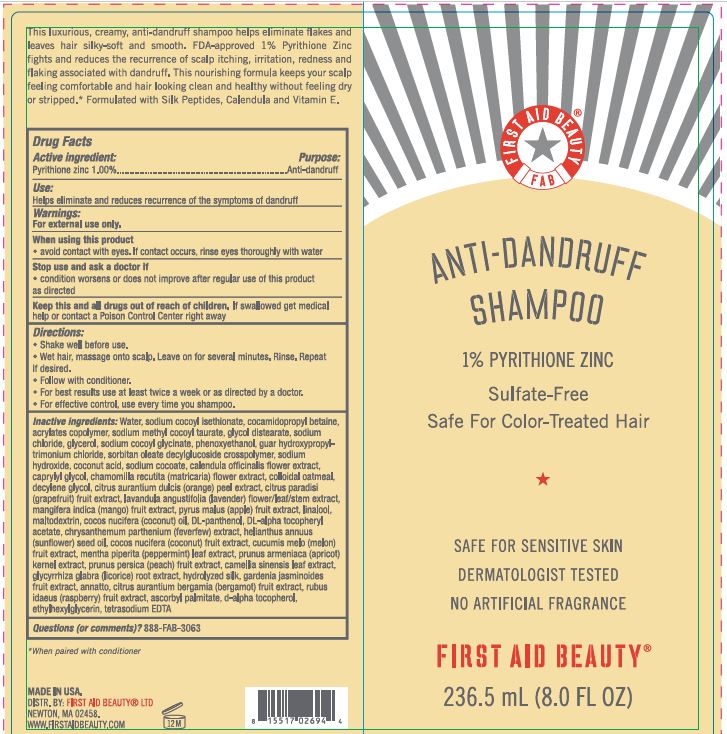 DRUG LABEL: First Aid Beauty Anti-Dandruff
NDC: 69423-591 | Form: SHAMPOO
Manufacturer: The Procter & Gamble Manufacturing Company
Category: otc | Type: HUMAN OTC DRUG LABEL
Date: 20251218

ACTIVE INGREDIENTS: PYRITHIONE ZINC 1 g/100 mL
INACTIVE INGREDIENTS: COCAMIDOPROPYL BETAINE; WATER; SODIUM COCOYL ISETHIONATE; ACRYLATES CROSSPOLYMER-6; GLYCOL DISTEARATE; SODIUM METHYL COCOYL TAURATE; SODIUM CHLORIDE; SODIUM COCOYL GLYCINATE; SODIUM HYDROXIDE; COCONUT ACID; SODIUM COCOATE; CALENDULA OFFICINALIS FLOWER; GUAR HYDROXYPROPYLTRIMONIUM CHLORIDE (1.7 SUBSTITUENTS PER SACCHARIDE); CAPRYLYL GLYCOL; CHAMOMILE; ORANGE PEEL; TANACETUM PARTHENIUM WHOLE; .ALPHA.-TOCOPHEROL ACETATE, DL-; COCONUT; SUNFLOWER OIL; MENTHA PIPERITA LEAF; PHENOXYETHANOL; PRUNUS ARMENIACA SEED; RASPBERRY; ASCORBYL PALMITATE; .ALPHA.-TOCOPHEROL, D-; MUSKMELON; ANNATTO; OATMEAL; MANGO; APPLE; LINALOOL, (+/-)-; MALTODEXTRIN; COCONUT OIL; PANTHENOL; GREEN TEA LEAF; GLYCYRRHIZA GLABRA; BERGAMOT OIL; ETHYLHEXYLGLYCERIN; EDETATE SODIUM; GLYCERIN; GARDENIA JASMINOIDES FRUIT; DECYLENE GLYCOL; GRAPEFRUIT; LAVANDULA ANGUSTIFOLIA FLOWERING TOP; GELATIN HYDROLYZATE (PORCINE SKIN, MW 3000); PEACH

First Aid Beauty Anti-Dandruff Shampoo

Drug Facts

Active ingredient

Pyrithione zinc 1.00%

Purpose

Anti-dandruff

Uses

helps eliminate and reduces recurrence of the symptoms of dandruff.

Warnings

For external use only.

When using this product

- avoid contact with eyes. If contact occurs, rinse eyes thoroughly with water.

Stop use and ask a doctor if

- condition worsens or does not improve after regular use of this product as directed.

KEEP OUT OF REACH OF CHILDREN

Keep this and all drugs out of reach of children. If swallowed, get medical help or contact a Poison Control Center right away.

Directions

- Shake before use.
- Wet hair, massage onto scalp. Leave on for several minutes. Rinse. Repeat if desired
- Follow with conditioner
- For best results use at least twice a week or as directed by a doctor
- For effective control, use every time you shampoo.

Inactive Ingredients

Water, sodium cocoyl isethionate, cocamidopropyl betaine, acrylates copolymer, sodium methyl cocoyl taurate, glycol distearate, sodium chloride, glycerol, sodium cocoyl glycinate, phenoxyethanol, guar hydroxypropyltrimonium chloride, sorbitan oleate decylglucoside crosspolymer, sodium hydroxide, coconut acid, sodium cocoate, calendula officinalis flower extract, caprylyl glycol, chamomilla recutita (matricaria) flower extract, colloidal oatmeal, decylene glycol, citrus aurentium dulcis (orange) peel extrect, citrus paredisi (grepefruit) fruit extract, lavandula angustifolia (lavender) flower􀀭eaf/stem extract, mangifera indica (mango) fruit extract, pyrus malus (apple) fruit extract, linalool, maltodextrin, cocos nucifera (coconut) oil, DL-panthenol, DL-alpha tocopheryl acetate, chrysanthemum parthenium (feverfew) extract, helianthus annuus (sunflower) seed oil, cocos nucifera (coconut) fruit extract, cucumis melo (melon) fruit extract, mentha piperita (peppermint) leaf extract, prunus armeniaca (apricot) kernel extract, prunus persica (peach) fruit extract, camellia sinensis leaf extract, glycyrrhiza glabra (licorice) root extract, hydrolyzed silk, gardenia jasminoides fruit extract, annafto, citrus aurantium bergamia (bergamot) fruit extract, rubus idaeus (respberry) fruit extract, ascorbyl palmitate, d-alpha tocopherol, ethylhexylglycerin, tetrasodium EDTA

Questions (or comments)?

888-FAB-3063

Dist. by FIRST AID BEAUTY LTD
Newton, MA 02458

PRINCIPAL DISPLAY PANEL - 236.5 mL Bottle Label

First Aid Beauty®

FAB

1% pyrithione zinc dandruff shampoo

Sulfate-Free

Safe For Color-Treated Hair

Safe for Sensitive Skin

Dermatologist Tested

No Artificial Fragrance

236.5 mL (8.0 FL OZ)